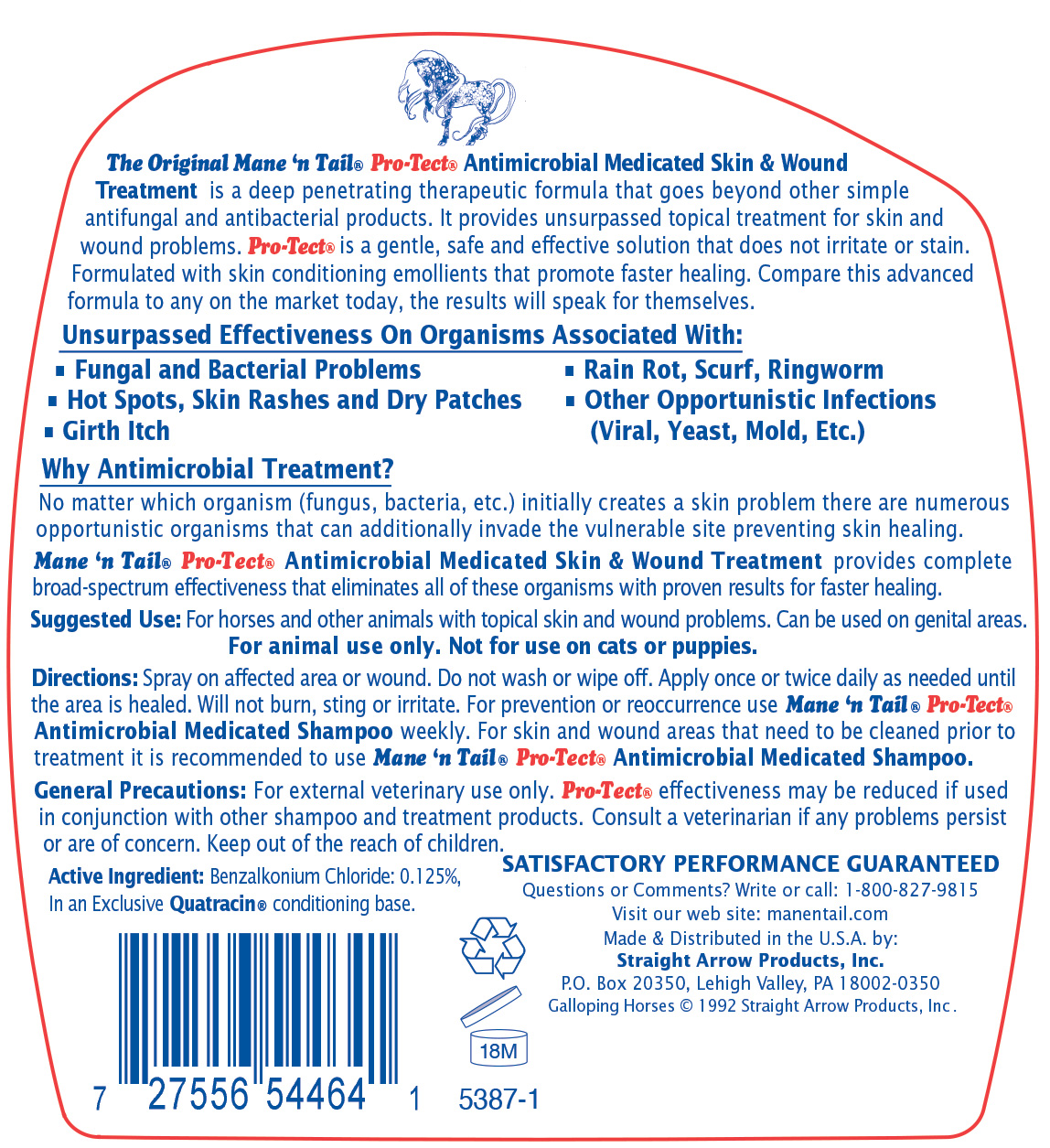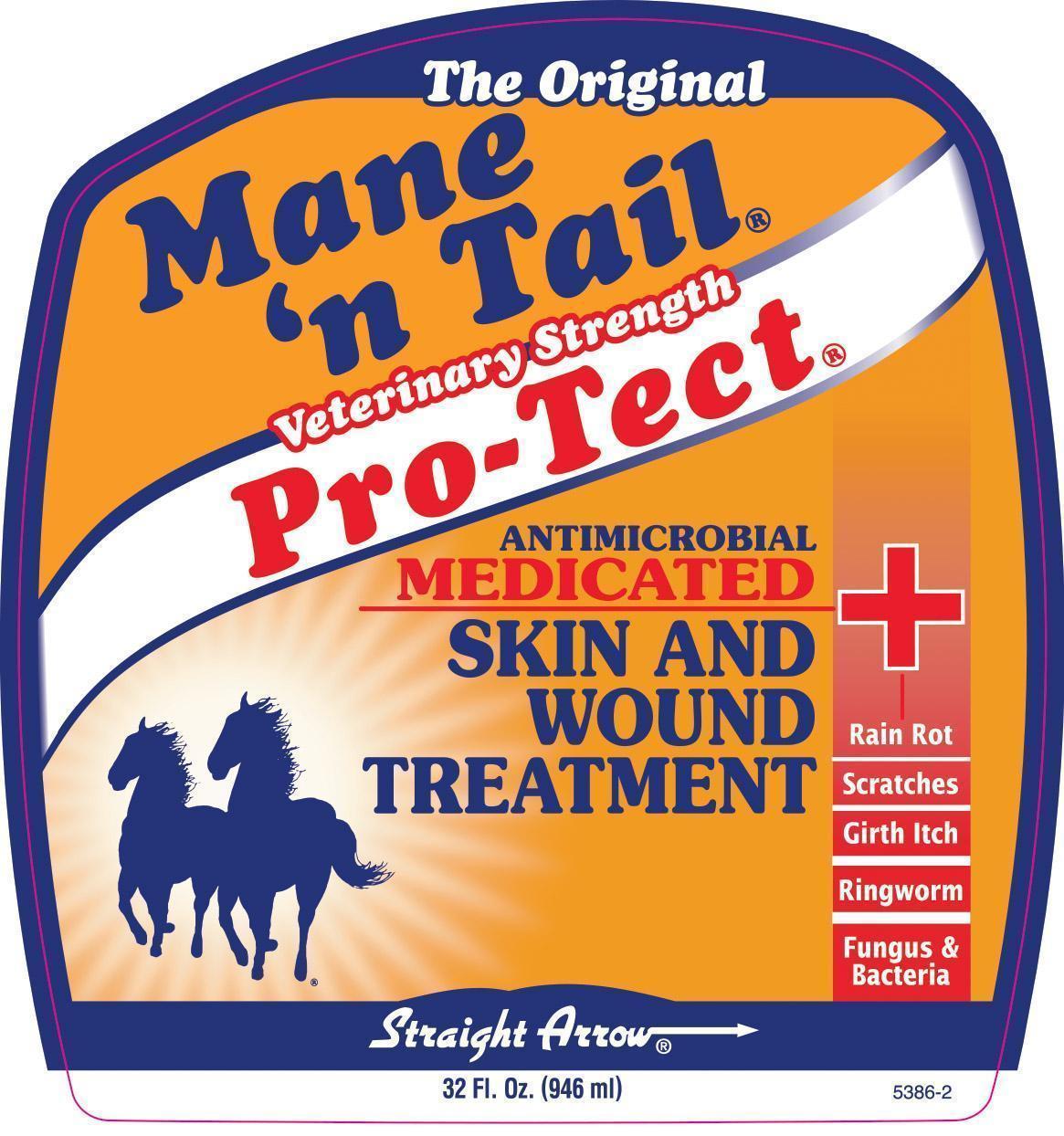 DRUG LABEL: Mane and Tail Veterinary Strength Pro-Tect Antimicrobial Skin and Wound Treatment
NDC: 62001-0335 | Form: LIQUID
Manufacturer: Straight Arrow Products, Inc.
Category: animal | Type: OTC ANIMAL DRUG LABEL
Date: 20250707

ACTIVE INGREDIENTS: BENZALKONIUM CHLORIDE .0015 g/1 g

Mane and Tail Veterinary Strength Pro-Tect Antimicrobial Skin and Wound Treatment

Active Ingredient Benzalkonium chloride 0.125% in an Exclusive Quatracin conditioning base.

PURPOSE

The Original Mane 'n Tail® Pro-Tect® Antimicrobial Medicated Skin & Wound Treatment is a deep penetrating therapeutic formula that goes beyond other simple antifungal and antibacterial products. It provides unsurpassed topical treatment for skin and wound problems. Pro-Tect® is a gentle, safe and effective solution that does not irritate or stain. Formulated with skin conditioning emollients that promote faster healing. Compare this advanced formula to any on the market today, the results will speak for themselves.

Unsurpassed Effectiveness On Organisms Associated With:

• Fungal and Bacterial Problems

• Hot Spots, Skin Rashes and Dry Patches

• Girth Itch

• Rain Rot, Scurf, Ringworm

• Other Opportunistic Infections (Viral, Yeast, Mold, Etc.)

Why Antimicrobial Treatment?

No matter which organism (fungus, bacteria, etc.) initially creates a skin problem there are numerous opportunistic organisms that can additionally invade the vulnerable site preventing skin healing.

Mane 'n Tail Pro-Tect® Antimicrobial Medicated Skin and Wound Treatment provides complete broad-spectrum effectiveness that eliminates all of these organisms with proven results for faster healing.

INDICATIONS AND USAGE

Suggested Use: For use on horses and other animals with topical skin and wound problems. Can be used on genital areas.

For animal use only. Not for use on cats or puppies.

Directions: Spray on affected area or wound. Do not wash or wipe off. Apply once or twice daily as needed until the area is healed. Will not burn, sting or irritate. For prevention or recurrence use Mane 'n Tail Pro-Tect Antimicrobial Medicated Shampoo weekly. For skin and wound areas that need to be cleaned prior to treatment it is recommended to use Mane 'n Tail Pro-Tect Antimicrobial Medicated Shampoo.

WARNINGS AND PRECAUTIONS

General Precautions: For external veterinary use only. Pro-Tect effectiveness may be reduced if used in conjunction with other shampoo and treatment products. Consult a veterinarian if any problems persist or are of concern. Keep out of the reach of children.